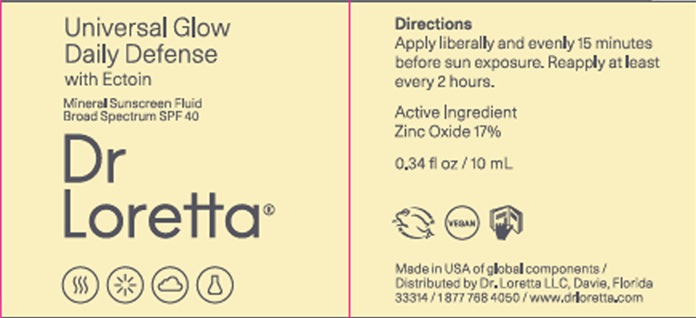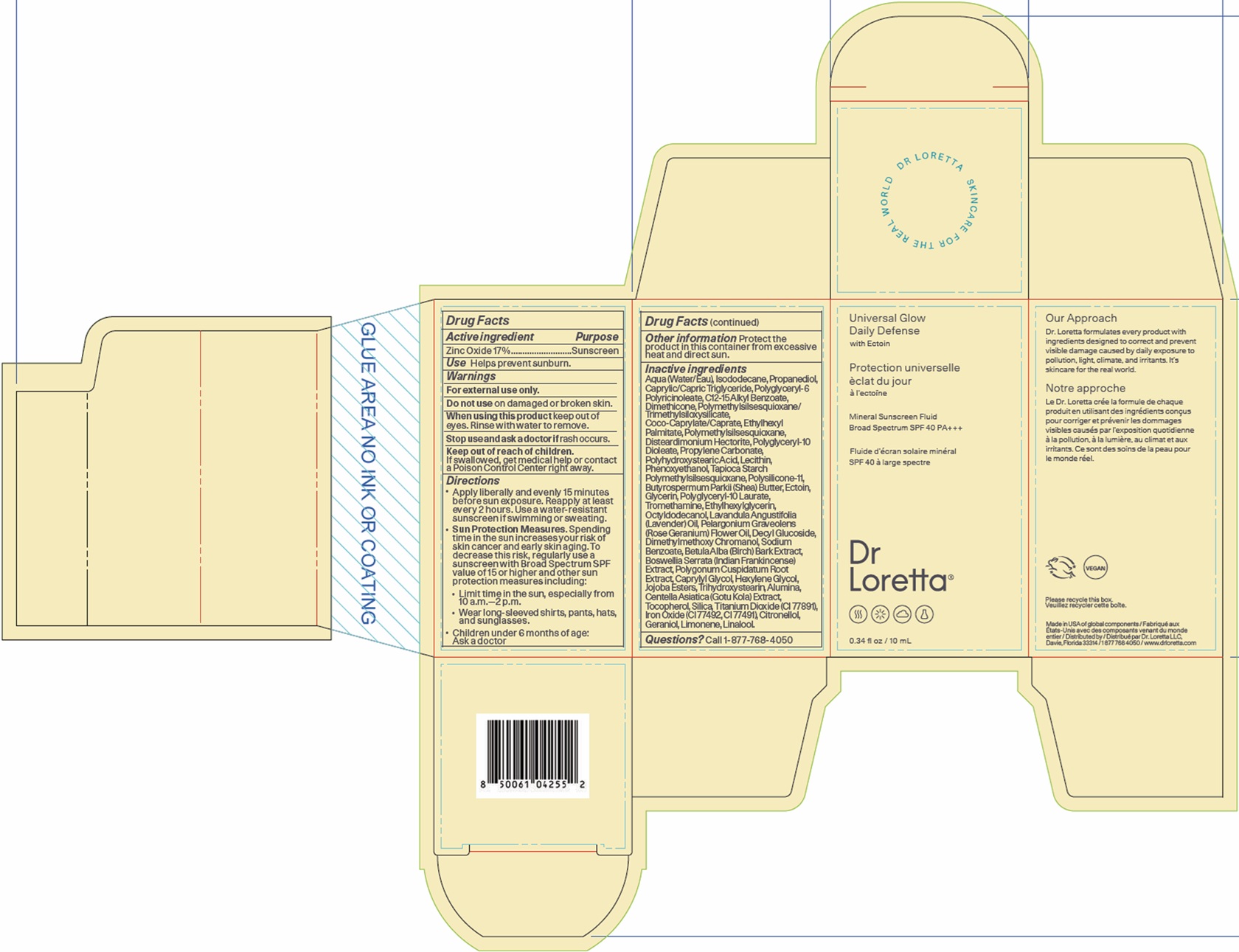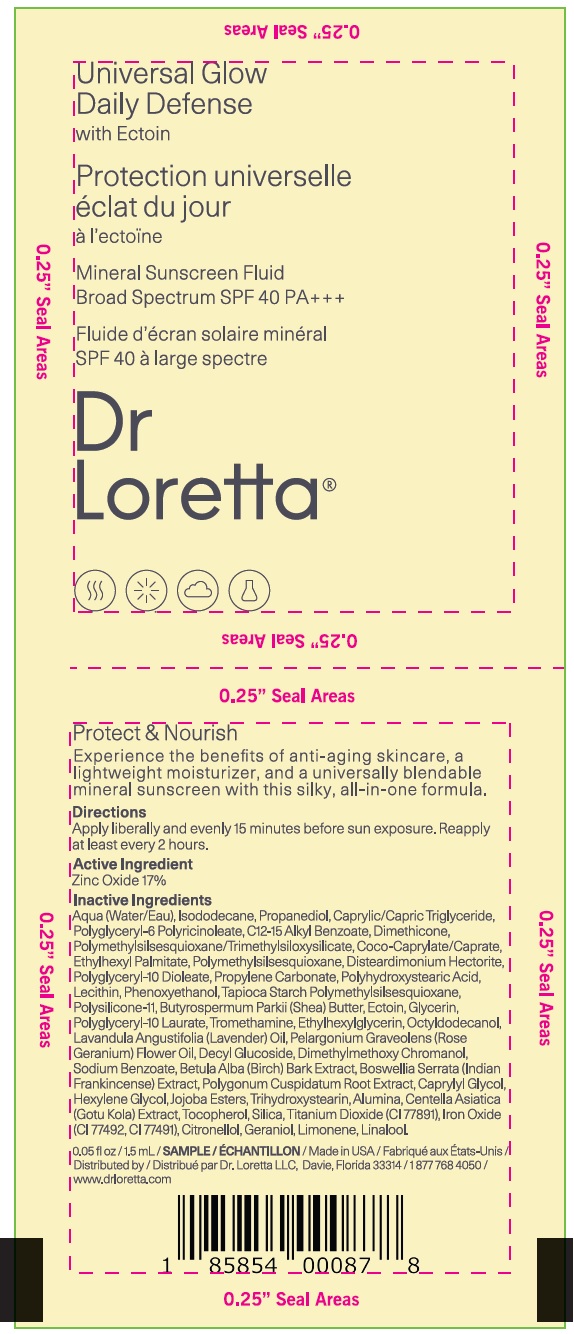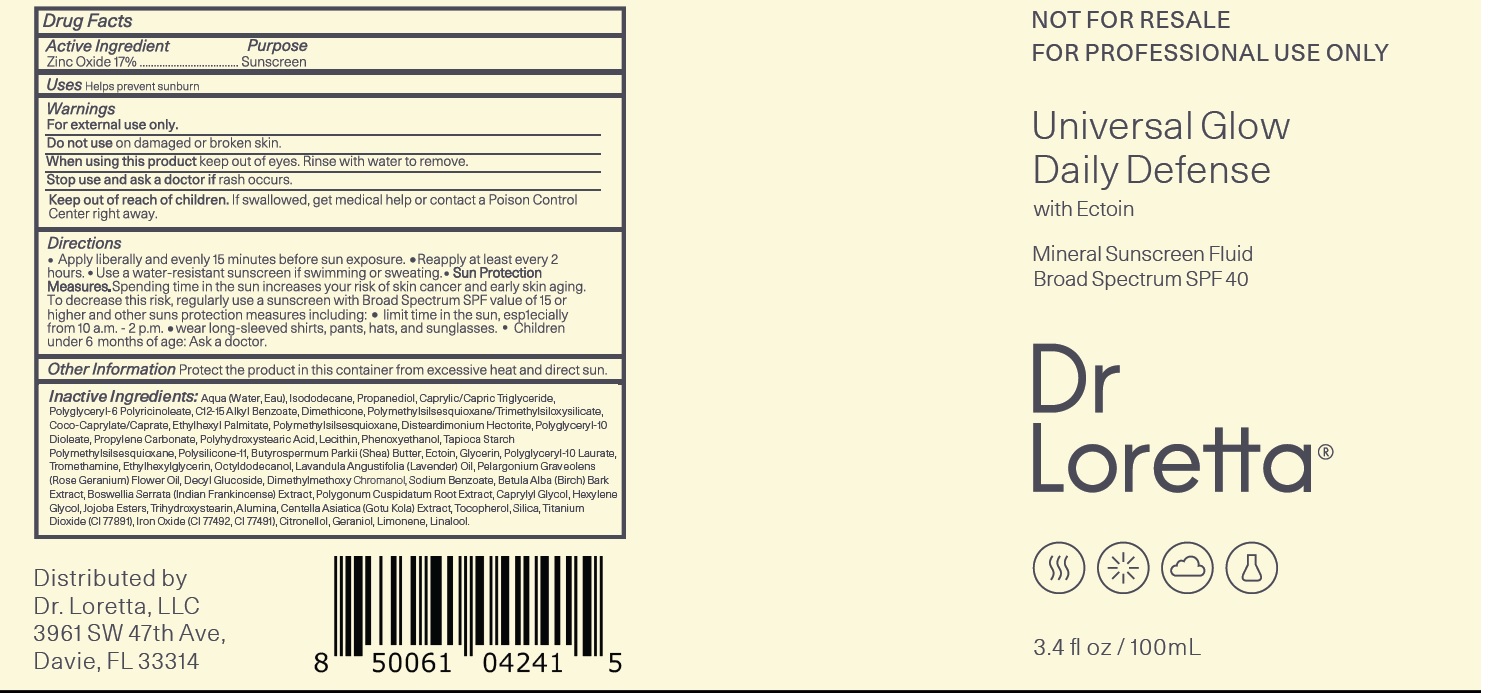 DRUG LABEL: Dr Loretta Universal Glow Daily Defense SPF 40
NDC: 71501-1910 | Form: CREAM
Manufacturer: Dr. Loretta, LLC
Category: otc | Type: HUMAN OTC DRUG LABEL
Date: 20260107

ACTIVE INGREDIENTS: ZINC OXIDE 170 mg/1 mL
INACTIVE INGREDIENTS: WATER; ISODODECANE; PROPANEDIOL; MEDIUM-CHAIN TRIGLYCERIDES; POLYGLYCERYL-6 POLYRICINOLEATE; ALKYL (C12-15) BENZOATE; DIMETHICONE; POLYMETHYLSILSESQUIOXANE/TRIMETHYLSILOXYSILICATE; COCOYL CAPRYLOCAPRATE; ETHYLHEXYL PALMITATE; POLYMETHYLSILSESQUIOXANE (4.5 MICRONS); DISTEARDIMONIUM HECTORITE; POLYGLYCERYL-10 DIOLEATE; PROPYLENE CARBONATE; PHENOXYETHANOL; DIMETHICONE/VINYL DIMETHICONE CROSSPOLYMER (SOFT PARTICLE); SHEA BUTTER; ECTOIN; GLYCERIN; POLYGLYCERYL-10 LAURATE; TROMETHAMINE; ETHYLHEXYLGLYCERIN; OCTYLDODECANOL; LAVENDER OIL; PELARGONIUM GRAVEOLENS FLOWER OIL; DECYL GLUCOSIDE; DIMETHYLMETHOXY CHROMANOL; SODIUM BENZOATE; BETULA PUBESCENS BARK; INDIAN FRANKINCENSE; REYNOUTRIA JAPONICA ROOT; CAPRYLYL GLYCOL; HEXYLENE GLYCOL; TRIHYDROXYSTEARIN; ALUMINUM OXIDE; CENTELLA ASIATICA TRITERPENOIDS; TOCOPHEROL; SILICON DIOXIDE; TITANIUM DIOXIDE; FERRIC OXIDE YELLOW; FERRIC OXIDE RED; .BETA.-CITRONELLOL, (R)-; GERANIOL; LIMONENE, (+)-; LINALOOL, (+/-)-

Dr Loretta Universal Glow Daily Defense SPF 40

Active Ingredient

Zinc Oxide 17%

Purpose

Sunscreen

Uses

Helps prevent sunburn

Warnings

For external use only.

Do not use

on damaged or broken skin.

When using this product

keep out of eyes. Rinse with water to remove.

Stop use and ask a doctor if

rash occurs.

Keep out of reach of children.

If swallowed, get medical help or contact a Poison Control Center right away.

Directions

- Apply liberally and evenly 15 minutes before sun exposure.
- Reapply at least every 2 hours.
- Use a water-resistant sunscreen if swimming or sweating.
- Sun Protection Measures.Spending time in the sun increases your risk of skin cancer and early skin aging. To decrease this risk, regularly use a sunscreen with Broad Spectrum SPF value of 15 or higher and other sun protection measures including:
- limit time in the sun, especially from 10 a.m.—2 p.m.
- wear long-sleeved shirts, pants, hats, and sunglasses.
- Children under 6 months of age: Ask a doctor.

Other Information

Protect the product in this container from excessive heat and direct sun.

Inactive Ingredients:

Aqua (Water, Eau), Isododecane, Propanediol, Caprylic/Capric Triglyceride, Polyglyceryl-6 Polyricinoleate, C12-15 Alkyl Benzoate, Dimethicone, Polymethylsilsesquioxane/Trimethylsiloxysilicate, Coco-Caprylate/Caprate, Ethylhexyl Palmitate, Polymethylsilsesquioxane, Disteardimonium Hectorite, Polyglyceryl-10 Dioleate, Propylene Carbonate, Polyhydroxystearic Acid, Lecithin, Phenoxyethanol, Tapioca Starch Polymethylsilsesquioxane, Polysilicone-11, Butyrospermum Parkii (Shea) Butter, Ectoin, Glycerin, Polyglyceryl-10 Laurate,Tromethamine, Ethylhexylglycerin, Octyldodecanol, Lavandula Angustifolia (Lavender) Oil, Pelargonium Graveolens (Rose Geranium) Flower Oil, Decyl Glucoside, Dimethylmethoxy Chromanol, Sodium Benzoate, Betula Alba (Birch) Bark Extract, Boswellia Serrata (Indian Frankincense) Extract, Polygonum Cuspidatum Root Extract, Caprylyl Glycol, Hexylene Glycol, Jojoba Esters, Trihydroxystearin, Alumina, Centella Asiatica (Gotu Kola) Extract, Tocopherol, Silica, Titanium Dioxide (CI 77891), Iron Oxide (CI 77492, CI 77491), Citronellol, Geraniol, Limonene, Linalool.